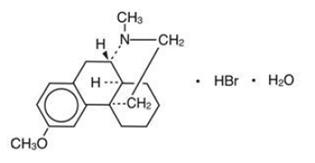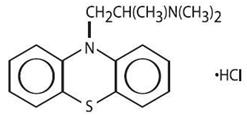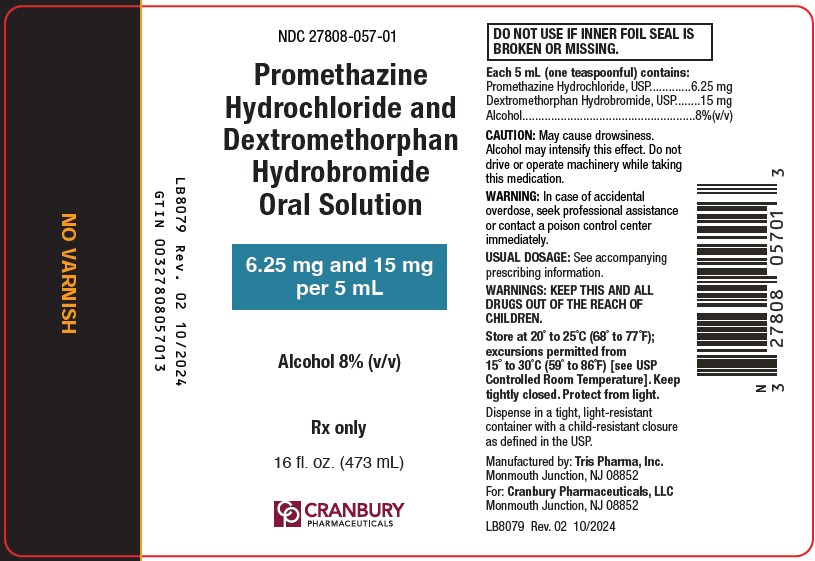 DRUG LABEL: Promethazine Hydrochloride and Dextromethorphan Hydrobromide
NDC: 27808-057 | Form: SOLUTION
Manufacturer: Cranbury Pharmaceuticals, LLC
Category: prescription | Type: HUMAN PRESCRIPTION DRUG LABEL
Date: 20251212

ACTIVE INGREDIENTS: PROMETHAZINE HYDROCHLORIDE 6.25 mg/5 mL; DEXTROMETHORPHAN HYDROBROMIDE 15 mg/5 mL
INACTIVE INGREDIENTS: ALCOHOL; ANHYDROUS CITRIC ACID; ASCORBIC ACID; EDETATE DISODIUM; FD&C YELLOW NO. 6; METHYLPARABEN; PROPYLENE GLYCOL; PROPYLPARABEN; SODIUM BENZOATE; SODIUM CITRATE; SACCHARIN SODIUM; SUCROSE; WATER

Promethazine Hydrochloride and Dextromethorphan Hydrobromide Oral Solution

DESCRIPTION

Each 5 mL (one teaspoonful), for oral administration contains: dextromethorphan hydrobromide 15 mg; promethazine hydrochloride 6.25 mg. Alcohol 8%(v/v).

Inactive Ingredients: anhydrous citric acid, ascorbic acid, edetate disodium, FD&C yellow No. 6, methylparaben, natural and artificial lemon mint flavor, propylene glycol, propylparaben, purified water, sodium benzoate, sodium citrate anhydrous, saccharin sodium, and sucrose.

Dextromethorphan hydrobromide is a salt of the methyl ether of the dextrorotatory isomer of levorphanol, a narcotic analgesic. It is chemically designated as 3-methoxy-17-methyl-9α, 13α, 14α-morphinan hydrobromide monohydrate. Dextromethorphan hydrobromide occurs as white crystals sparingly soluble in water and freely soluble in alcohol. It has a molecular weight of 370.32, a molecular formula of C18H25NO•HBr•H2O, and the following structural formula:

Promethazine is a racemic compound. Promethazine hydrochloride, a phenothiazine derivative, is chemically designated as 10H-Phenothiazine-10-ethanamine, N,N, α-trimethyl-, monohydrochloride.

Promethazine hydrochloride occurs as a white to faint yellow, practically odorless, crystalline powder which slowly oxidizes and turns blue on prolonged exposure to air. It is soluble in water and freely soluble in alcohol. It has a molecular weight of 320.88, a molecular formula of C17H20N2S•HCl, and the following structural formula:

CLINICAL PHARMACOLOGY

Dextromethorphan: Dextromethorphan is an antitussive agent and, unlike the isomeric levorphanol, it has no analgesic or addictive properties.

The drug acts centrally and elevates the threshold for coughing. It is about equal to codeine in depressing the cough reflex. In therapeutic dosage dextromethorphan does not inhibit ciliary activity.

Dextromethorphan is rapidly absorbed from the gastrointestinal tract and exerts its effect in 15 to 30 minutes. The duration of action after oral administration is approximately three to six hours. Dextromethorphan is metabolized primarily by liver enzymes undergoing O-demethylation, N-demethylation, and partial conjugation with glucuronic acid and sulfate. In humans, (+)-3-hydroxy-N-methyl-morphinan, (+)-3-hydroxymorphinan, and traces of unmetabolized drug were found in urine after oral administration.

Promethazine: Promethazine is a phenothiazine derivative which differs structurally from the antipsychotic phenothiazines by the presence of a branched side chain and no ring substitution. It is thought that this configuration is responsible for its relative lack (1/10 that of chlorpromazine) of dopamine antagonist properties.

Promethazine is an H1 receptor blocking agent. In addition to its antihistaminic action, it provides clinically useful sedative and antiemetic effects.

Promethazine is well absorbed from the gastrointestinal tract. Clinical effects are apparent within 20 minutes after oral administration and generally last four to six hours, although they may persist as long as 12 hours. Promethazine is metabolized by the liver to a variety of compounds; the sulfoxides of promethazine and N-demethylpromethazine are the predominant metabolites appearing in the urine.

INDICATIONS AND USAGE

Promethazine Hydrochloride and Dextromethorphan Hydrobromide Oral Solution is indicated for the temporary relief of coughs and upper respiratory symptoms associated with allergy or the common cold.

CONTRAINDICATIONS

Promethazine Hydrochloride and Dextromethorphan Hydrobromide Oral Solution is contraindicated for use in pediatric patients less than two years of age.

Dextromethorphan should not be used in patients receiving a monoamine oxidase inhibitor (MAOI) (see PRECAUTIONS, Drug Interactions).

Promethazine is contraindicated in comatose states, and in individuals known to be hypersensitive or to have had an idiosyncratic reaction to promethazine or to other phenothiazines.

Antihistamines are contraindicated for use in the treatment of lower respiratory tract symptoms, including asthma.

WARNINGS

WARNING

PROMETHAZINE HYDROCHLORIDE SHOULD NOT BE USED IN PEDIATRIC PATIENTS LESS THAN 2 YEARS OF AGE BECAUSE OF THE POTENTIAL FOR FATAL RESPIRATORY DEPRESSION.

POSTMARKETING CASES OF RESPIRATORY DEPRESSION, INCLUDING FATALITIES, HAVE BEEN REPORTED WITH USE OF PROMETHAZINE HYDROCHLORIDE IN PEDIATRIC PATIENTS LESS THAN 2 YEARS OF AGE. A WIDE RANGE OF WEIGHT-BASED DOSES OF PROMETHAZINE HYDROCHLORIDE HAVE RESULTED IN RESPIRATORY DEPRESSION IN THESE PATIENTS.

CAUTION SHOULD BE EXERCISED WHEN ADMINISTERING PROMETHAZINE HYDROCHLORIDE TO PEDIATRIC PATIENTS 2 YEARS OF AGE AND OLDER. IT IS RECOMMENDED THAT THE LOWEST EFFECTIVE DOSE OF PROMETHAZINE HYDROCHLORIDE BE USED IN PEDIATRIC PATIENTS 2 YEARS OF AGE AND OLDER AND CONCOMITANT ADMINISTRATION OF OTHER DRUGS WITH RESPIRATORY DEPRESSANT EFFECTS BE AVOIDED.

Dextromethorphan: Administration of dextromethorphan may be accompanied by histamine release and should be used with caution in atopic children.

Promethazine:

CNS Depression

Promethazine may impair the mental and/or physical abilities required for the performance of potentially hazardous tasks, such as driving a vehicle or operating machinery. The impairment may be amplified by concomitant use of other central-nervous-system depressants such as alcohol, sedatives/hypnotics (including barbiturates), narcotics, narcotic analgesics, general anesthetics, tricyclic antidepressants, and tranquilizers; therefore such agents should either be eliminated or given in reduced dosage in the presence of promethazine HCl (see PRECAUTIONS-Information for Patients and Drug Interactions).

Respiratory Depression

Promethazine may lead to potentially fatal respiratory depression.

Use of promethazine in patients with compromised respiratory function (e.g., COPD, sleep apnea) should be avoided.

Lower Seizure Threshold

Promethazine may lower seizure threshold. It should be used with caution in persons with seizure disorders or in persons who are using concomitant medications, such as narcotics or local anesthetics, which may also affect seizure threshold.

Bone-Marrow Depression

Promethazine should be used with caution in patients with bone-marrow depression. Leukopenia and agranulocytosis have been reported, usually when promethazine HCl has been used in association with other known marrow-toxic agents.

Neuroleptic Malignant Syndrome

A potentially fatal symptom complex sometimes referred to as Neuroleptic Malignant Syndrome (NMS) has been reported in association with promethazine HCl alone or in combination with antipsychotic drugs. Clinical manifestations of NMS are hyperpyrexia, muscle rigidity, altered mental status and evidence of autonomic instability (irregular pulse or blood pressure, tachycardia, diaphoresis and cardiac dysrhythmias).

The diagnostic evaluation of patients with this syndrome is complicated. In arriving at a diagnosis, it is important to identify cases where the clinical presentation includes both serious medical illness (e.g. pneumonia, systemic infection, etc.) and untreated or inadequately treated extrapyramidal signs and symptoms (EPS). Other important considerations in the differential diagnosis include central anticholinergic toxicity, heat stroke, drug fever and primary central nervous system (CNS) pathology.

The management of NMS should include 1) immediate discontinuation of promethazine HCl, antipsychotic drugs, if any, and other drugs not essential to concurrent therapy, 2) intensive symptomatic treatment and medical monitoring, and 3) treatment of any concomitant serious medical problems for which specific treatments are available. There is no general agreement about specific pharmacological treatment regimens for uncomplicated NMS.

Since recurrences of NMS have been reported with phenothiazines, the reintroduction of promethazine HCl should be carefully considered.

Use In Pediatric Patients

PROMETHAZINE PRODUCTS ARE CONTRAINDICATED FOR USE IN PEDIATRIC PATIENTS LESS THAN TWO YEARS OF AGE.

CAUTION SHOULD BE EXERCISED WHEN ADMINISTERING PROMETHAZINE PRODUCTS TO PEDIATRIC PATIENTS 2 YEARS OF AGE AND OLDER BECAUSE OF THE POTENTIAL FOR FATAL RESPIRATORY DEPRESSION. RESPIRATORY DEPRESSION AND APNEA, SOMETIMES ASSOCIATED WITH DEATH, ARE STRONGLY ASSOCIATED WITH PROMETHAZINE PRODUCTS AND ARE NOT DIRECTLY RELATED TO INDIVIDUALIZED WEIGHT-BASED DOSING, WHICH MIGHT OTHERWISE PERMIT SAFE ADMINISTRATION. CONCOMITANT ADMINISTRATION OF PROMETHAZINE PRODUCTS WITH OTHER RESPIRATORY DEPRESSANTS HAS AN ASSOCIATION WITH RESPIRATORY DEPRESSION, AND SOMETIMES DEATH, IN PEDIATRIC PATIENTS.

ANTIEMETICS ARE NOT RECOMMENDED FOR TREATMENT OF UNCOMPLICATED VOMITING IN PEDIATRIC PATIENTS, AND THEIR USE SHOULD BE LIMITED TO PROLONGED VOMITING OF KNOWN ETIOLOGY. THE EXTRAPYRAMIDAL SYMPTOMS WHICH CAN OCCUR SECONDARY TO PROMETHAZINE HYDROCHLORIDE ADMINISTRATION MAY BE CONFUSED WITH THE CNS SIGNS OF UNDIAGNOSED PRIMARY DISEASE, e.g., ENCEPHALOPATHY OR REYE’S SYNDROME. THE USE OF PROMETHAZINE PRODUCTS SHOULD BE AVOIDED IN PEDIATRIC PATIENTS WHOSE SIGNS AND SYMPTOMS MAY SUGGEST REYE’S SYNDROME OR OTHER HEPATIC DISEASES.

Excessively large dosages of antihistamines, including promethazine hydrochloride, in pediatric patients may cause sudden death (see OVERDOSAGE). Hallucinations and convulsions have occurred with therapeutic doses and overdoses of promethazine hydrochloride in pediatric patients. In pediatric patients who are acutely ill associated with dehydration, there is an increased susceptibility to dystonias with the use of promethazine HCl.

Other Consideration:

Administration of promethazine has been associated with reported cholestatic jaundice.

PRECAUTIONS

Animal reproduction studies have not been conducted with the drug combination–promethazine and dextromethorphan. It is not known whether this drug combination can cause fetal harm when administered to a pregnant woman or can affect reproduction capacity. Promethazine and dextromethorphan should be given to a pregnant woman only if clearly needed.

General

Dextromethorphan should be used with caution in sedated patients, in the debilitated, and in patients confined to the supine position.

Drugs having anticholinergic properties should be used with caution in patients with narrow-angle glaucoma, prostatic hypertrophy, stenosing peptic ulcer, pyloroduodenal obstruction, and bladder-neck obstruction.

Promethazine should be used cautiously in persons with cardiovascular disease or with impairment of liver function.

Information for Patients

Patients should be advised to measure Promethazine Hydrochloride and Dextromethorphan Hydrobromide Oral Solution with an accurate measuring device. A household teaspoon is not an accurate measuring device and could lead to overdosage, especially when a half a teaspoon is measured. A pharmacist can recommend an appropriate measuring device and can provide instructions for measuring the correct dose.

Promethazine and dextromethorphan may cause marked drowsiness or impair the mental and/or physical abilities required for the performance of potentially hazardous tasks, such as driving a vehicle or operating machinery. Ambulatory patients should be told to avoid engaging in such activities until it is known that they do not become drowsy or dizzy from promethazine and dextromethorphan therapy. Children should be supervised to avoid potential harm in bike riding or in other hazardous activities.

The concomitant use of alcohol or other central-nervous-system depressants, such as sedatives/hypnotics (including barbiturates), narcotics, narcotic analgesics, general anesthetics, tricyclic antidepressants, and tranquilizers, may enhance impairment (see WARNINGS – CNS Depression and PRECAUTIONS – Drug Interactions).

Patients should be advised to report any involuntary muscle movements.

Avoid prolonged exposure to the sun.

Drug Interactions

Dextromethorphan: Hyperpyrexia, hypotension, and death have been reported coincident with the coadministration of monoamine oxidase (MAO) inhibitors and products containing dextromethorphan. Thus, concomitant administration of promethazine with dextromethorphan and MAO inhibitors should be avoided (see CONTRAINDICATIONS).

Promethazine:

CNS Depressants - Promethazine may increase, prolong, or intensify the sedative action of other central-nervous-system depressants, such as alcohol, sedatives/hypnotics (including barbiturates), narcotics, narcotic analgesics, general anesthetics, tricyclic antidepressants, and tranquilizers; therefore, such agents should be avoided or administered in reduced dosage to patients receiving promethazine. When given concomitantly with promethazine, the dose of barbiturates should be reduced by at least one-half, and the dose of narcotics should be reduced by one-quarter to one-half. Dosage must be individualized. Excessive amounts of promethazine HCl relative to a narcotic may lead to restlessness and motor hyperactivity in the patient with pain; these symptoms usually disappear with adequate control of the pain.

Epinephrine - Because of the potential for promethazine to reverse epinephrine’s vasopressor effect, epinephrine should NOT be used to treat hypotension associated with promethazine overdose.

Anticholinergics - Concomitant use of other agents with anticholinergic properties should be undertaken with caution.

Monoamine oxidase inhibitors (MAOI) - Drug interactions, including an increased incidence of extrapyramidal effects, have been reported when some MAOI and phenothiazines are used concomitantly.

Drug/Laboratory Test Interactions

The following laboratory tests may be affected in patients who are receiving therapy with promethazine hydrochloride:

Pregnancy Tests: Diagnostic pregnancy tests based on immunological reactions between HCG and anti-HCG may result in false-negative or false-positive interpretations.

Glucose Tolerance Test: An increase in blood glucose has been reported in patients receiving promethazine.

Carcinogenesis, Mutagenesis, Impairment of Fertility

Long-term animal studies have not been performed to assess the carcinogenic potential of promethazine or of dextromethorphan. There are no animal or human data concerning the carcinogenicity, mutagenicity, or impairment of fertility with these drugs. Promethazine was nonmutagenic in the Salmonella test system of Ames.

Pregnancy

Teratogenic Effects

Teratogenic effects have not been demonstrated in rat-feeding studies at doses of 6.25 and 12.5 mg/kg of promethazine HCl. These doses are from approximately 2.1 to 4.2 times the maximum recommended total daily dose of promethazine for a 50-kg subject, depending upon the indication for which the drug is prescribed. Daily doses of 25 mg/kg intraperitoneally have been found to produce fetal mortality in rats.

Specific studies to test the action of the drug on parturition, lactation, and development of the animal neonate were not done, but a general preliminary study in rats indicated no effect on these parameters. Although antihistamines have been found to produce fetal mortality in rodents, the pharmacological effects of histamine in the rodent do not parallel those in man. There are no adequate and well-controlled studies of promethazine in pregnant women.

Promethazine and dextromethorphan should be used during pregnancy only if the potential benefit justifies the risk to the fetus.

Nonteratogenic Effects

Promethazine administered to a pregnant woman within two weeks of delivery may inhibit platelet aggregation in the newborn.

Labor and Delivery

Limited data suggest that use of promethazine HCl during labor and delivery does not have an appreciable effect on the duration of labor or delivery and does not increase the risk of need for intervention in the newborn. The effect on later growth and development of the newborn is unknown. See also “Nonteratogenic Effects”.

Nursing Mothers

It is not known whether promethazine or dextromethorphan is excreted in human milk.

Caution should be exercised when promethazine and dextromethorphan is administered to a nursing woman.

Pediatric Use

PROMETHAZINE HYDROCHLORIDE AND DEXTROMETHORPHAN HYDROBROMIDE ORAL SOLUTION IS CONTRAINDICATED FOR USE IN PEDIATRIC PATIENTS LESS THAN TWO YEARS OF AGE (see WARNINGS – Black Box Warning and Use in Pediatric Patients).

Promethazine Hydrochloride and Dextromethorphan Hydrobromide Oral Solution should be used with caution in pediatric patients 2 years of age and older (seeWARNINGS – Use in Pediatric Patients).

Geriatric Use

Clinical studies of Promethazine Hydrochloride and Dextromethorphan Hydrobromide Oral Solution did not include sufficient numbers of subjects aged 65 and over to determine whether they respond differently from younger subjects. Other reported clinical experience has not identified differences in responses between the elderly and younger patients. In general, dose selection for an elderly patient should be cautious, usually starting at the low end of the dosing range, reflecting the greater frequency of decreased hepatic, renal or cardiac function, and of concomitant disease or other drug therapy.

Sedating drugs may cause confusion and over-sedation in the elderly; elderly patients generally should be started on low doses of Promethazine Hydrochloride and Dextromethorphan Hydrobromide Oral Solution and observed closely.

ADVERSE REACTIONS

Dextromethorphan: Dextromethorphan hydrobromide occasionally causes slight drowsiness, dizziness, and gastrointestinal disturbances.

Promethazine: Central Nervous System - Drowsiness is the most prominent CNS effect of this drug. Sedation, somnolence, blurred vision, dizziness; confusion, disorientation, and extrapyramidal symptoms such as oculogyric crisis, torticollis, and tongue protrusion; lassitude, tinnitus, incoordination, fatigue, euphoria, nervousness, diplopia, insomnia, tremors, convulsive seizures, excitation, catatonic-like states, hysteria. Hallucinations have also been reported.

Cardiovascular - Increased or decreased blood pressure, tachycardia, bradycardia, faintness.

Dermatologic - Dermatitis, photosensitivity, urticaria.

Hematologic - Leukopenia, thrombocytopenia, thrombocytopenic purpura, agranulocytosis.

Gastrointestinal - Dry mouth, nausea, vomiting, jaundice.

Respiratory - Asthma, nasal stuffiness, respiratory depression (potentially fatal) and apnea (potentially fatal) (see WARNINGS-Promethazine; Respiratory Depression).

Other - Angioneurotic edema. Neuroleptic malignant syndrome (potentially fatal) has also been reported (see WARNINGS-Promethazine; Neuroleptic Malignant Syndrome).

Paradoxical Reactions - Hyperexcitability and abnormal movements have been reported in patients following a single administration of promethazine HCl. Consideration should be given to the discontinuation of promethazine HCl and to the use of other drugs if these reactions occur. Respiratory depression, nightmares, delirium, and agitated behavior have also been reported in some of these patients.

DRUG ABUSE AND DEPENDENCE

According to the WHO Expert Committee on Drug Dependence, dextromethorphan could produce very slight psychic dependence but no physical dependence.

OVERDOSAGE

Dextromethorphan: Dextromethorphan may produce central excitement and mental confusion. Very high doses may produce respiratory depression. One case of toxic psychosis (hyperactivity, marked visual and auditory hallucinations) after ingestion of a single dose of 20 tablets (300 mg) of dextromethorphan has been reported.

Promethazine: Signs and symptoms of overdosage with promethazine HCl range from mild depression of the central nervous system and cardiovascular system to profound hypotension, respiratory depression, unconsciousness, and sudden death. Other reported reactions include hyperreflexia, hypertonia, ataxia, athetosis, and extensor-plantar reflexes (Babinski reflex).

Stimulation may be evident, especially in children and geriatric patients. Convulsions may rarely occur. A paradoxical reaction has been reported in children receiving single doses of 75 mg to 125 mg orally, characterized by hyperexcitability and nightmares.

Atropine-like signs and symptoms–dry mouth, fixed dilated pupils, flushing, as well as gastrointestinal symptoms, may occur.

Treatment: The treatment of overdosage with promethazine and dextromethorphan is essentially symptomatic and supportive. Only in cases of extreme overdosage or individual sensitivity do vital signs including respiration, pulse, blood pressure, temperature, and EKG need to be monitored. Activated charcoal orally or by lavage may be given, or sodium or magnesium sulfate orally as a cathartic. Attention should be given to the reestablishment of adequate respiratory exchange through provision of a patent airway and institution of assisted or controlled ventilation. Diazepam may be used to control convulsions. Acidosis and electrolyte losses should be corrected. The antidotal efficacy of narcotic antagonists to dextromethorphan has not been established; note that any of the depressant effects of promethazine are not reversed by naloxone. Avoid analeptics, which may cause convulsions.

The treatment of choice for resulting hypotension is administration of intravenous fluids, accompanied by repositioning if indicated. In the event that vasopressors are considered for the management of severe hypotension which does not respond to intravenous fluids and repositioning, the administration of norepinephrine or phenylephrine should be considered. EPINEPHRINE SHOULD NOT BE USED, since its use in a patient with partial adrenergic blockade may further lower the blood pressure. Extrapyramidal reactions may be treated with anticholinergic antiparkinson agents, diphenhydramine, or barbiturates. Oxygen may also be administered.

Limited experience with dialysis indicates that it is not helpful.

DOSAGE AND ADMINISTRATION

It is important that Promethazine Hydrochloride and Dextromethorphan Hydrobromide Oral Solution is measured with an accurate measuring device (see PRECAUTIONS-Information for Patients). A household teaspoon is not an accurate measuring device and could lead to overdosage, especially when half a teaspoon is to be measured. It is strongly recommended that an accurate measuring device be used. A pharmacist can provide an appropriate device and can provide instructions for measuring the correct dose.

Promethazine Hydrochloride and Dextromethorphan Hydrobromide Oral Solution is contraindicated for children under 2 years of age (see WARNINGS Black Box Warning and Use in Pediatric Patients).

The average effective dose is given in the following table:
Adults | 1 teaspoonful (5 mL) every 4 to 6 hours, not to exceed 30 mL in 24 hours.
Children 6 years to under 12 years | ½ to 1 teaspoonful (2.5 to 5 mL) every 4 to 6 hours, not to exceed 20 mL in 24 hours.
Children 2 years to under 6 years | ¼ to ½ teaspoonful (1.25 to 2.5 mL) every 4 to 6 hours, not to exceed 10 mL in 24 hours.

HOW SUPPLIED

This preparation is a yellow to amber colored lemon-mint flavored oral solution, containing promethazine hydrochloride 6.25 mg/5 mL, dextromethorphan hydrobromide 15 mg/5 mL and alcohol 8 percent, and is available in 16 fl. oz. (473 mL) bottles, (NDC 27808-057-01).

Keep tightly closed. Protect from light.

Store at 20° to 25°C (68° to 77°F); excursions permitted from 15° to 30°C (59° to 86°F) [see USP Controlled Room Temperature].

Dispense in a tight, light-resistant container with a child-resistant closure as defined in the USP.

Manufactured By:
Tris Pharma, Inc.
Monmouth Junction, NJ 08852

For:
Cranbury Pharmaceuticals, LLC
Monmouth Junction, NJ 08852

LB8077

Rev. 02

10/2024

PACKAGE LABEL.PRINCIPAL DISPLAY PANEL

NDC 27808-057-01

Promethazine Hydrochloride and Dextromethorphan Hydrobromide Oral Solution

6.25 mg and 15 mg per 5 mL

Alcohol 8% (v/v)

Rx only

16 fl. oz. (473 mL)